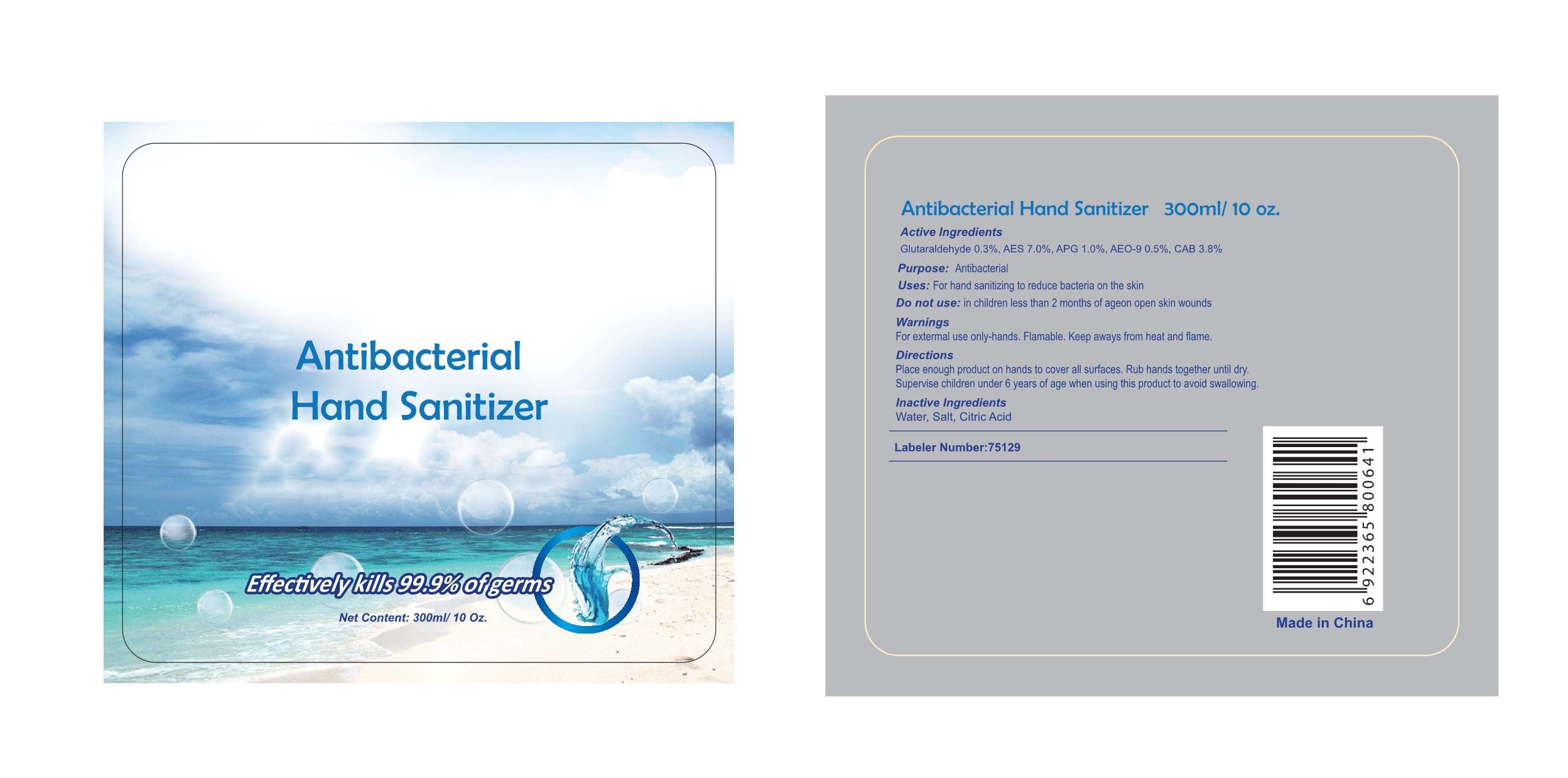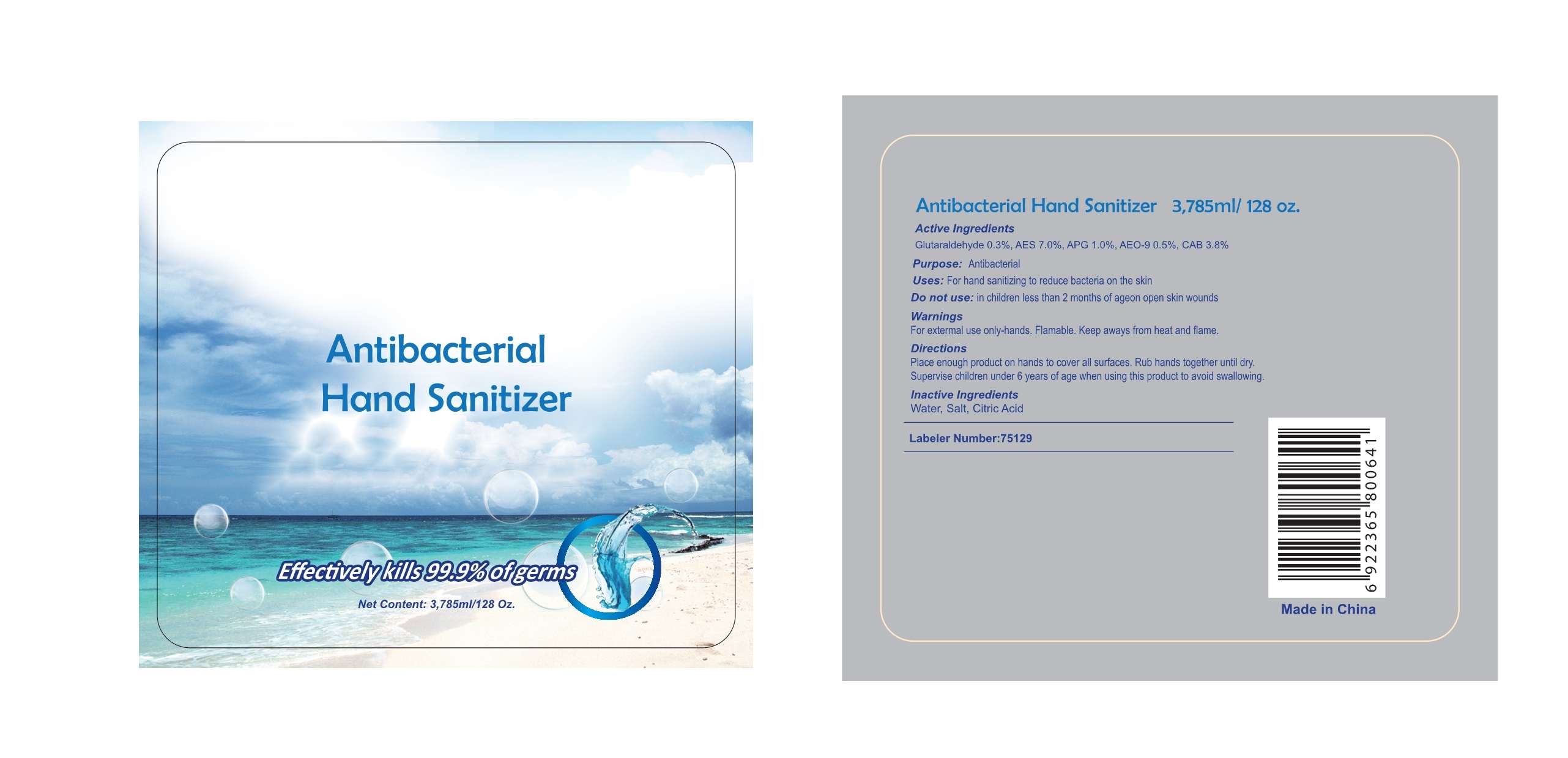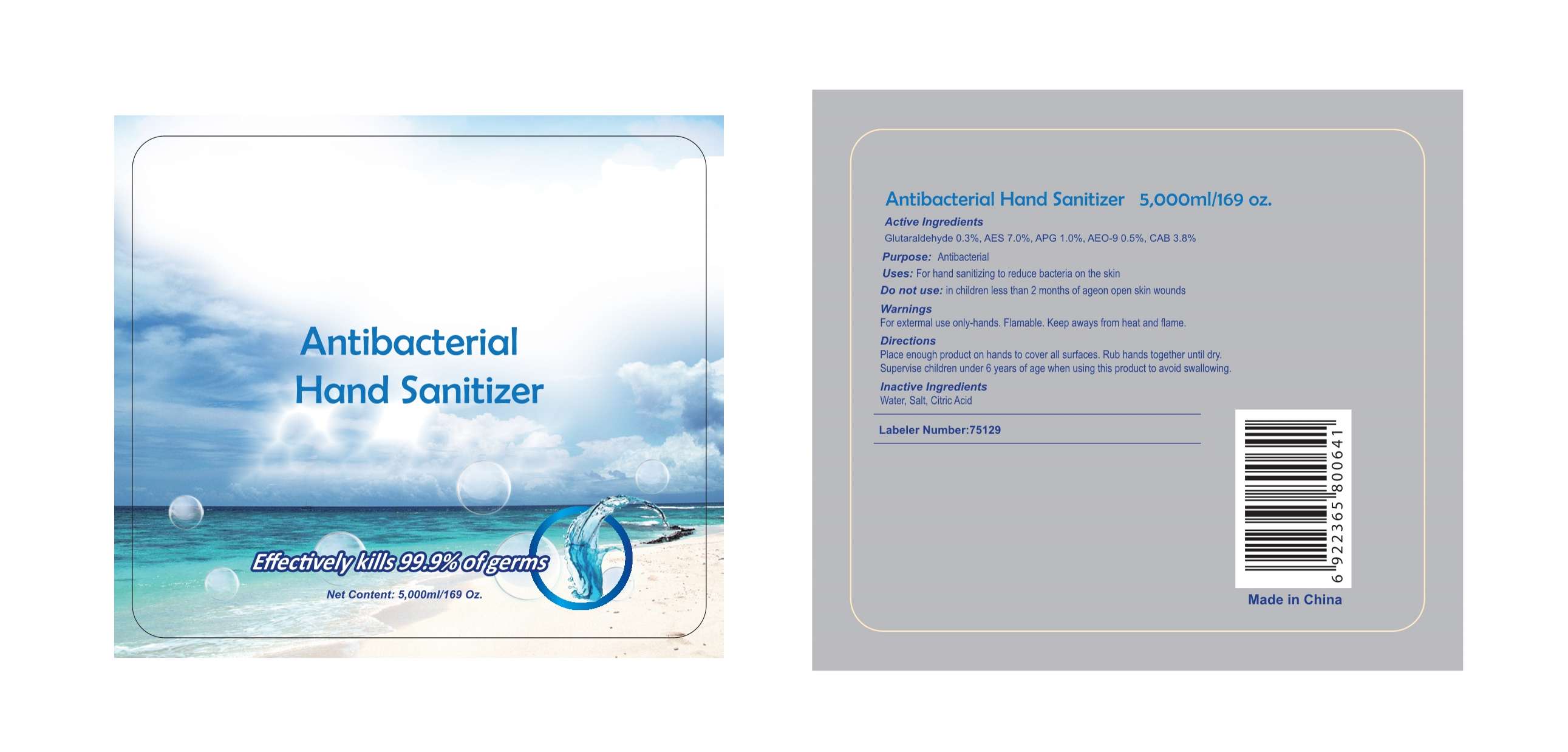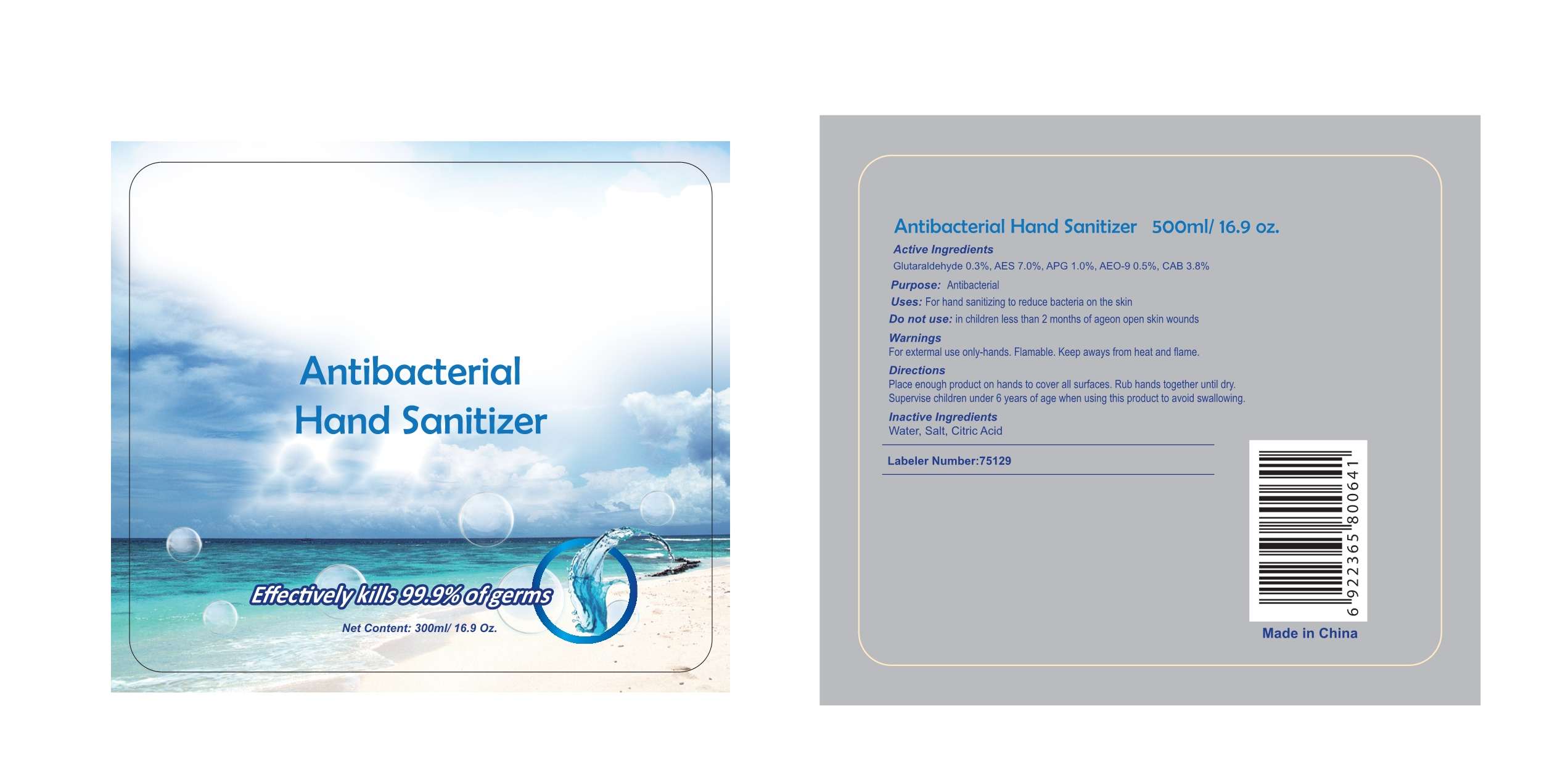 DRUG LABEL: Antibacterial  Hand Sanitizer
NDC: 75129-002 | Form: GEL
Manufacturer: Shanghai Rayshine ENVI-TECH Developing CO., Ltd.
Category: otc | Type: HUMAN OTC DRUG LABEL
Date: 20200418

ACTIVE INGREDIENTS: GLUTARAL 0.3 g/100 mL; CARBONIC ANHYDRASE 1 3.8 g/100 mL
INACTIVE INGREDIENTS: WATER; SODIUM CHLORIDE; CITRIC ACID MONOHYDRATE

Antibacterial Hand Sanitizer

Active Ingredients

Glutaraldehyde 0.3%, AES 7.0%, APG 1.0%, AEO-9 0.5%, CAB 3.8%

Purpose

Antibacterial

Uses

For hand sanitizing to reduce bacteria on the skin.

Warnings

For extermal use only-hands. Flamable. Keep aways from heat and flame.

Do not use

in children less than 2 months of ageon open skin wounds

Directions

Place enough product on hands to cover all surfaces. Rub hands together until dry.
Supervise children under 6 years of age when using this product to avoid swallowing.

Inactive Ingredients

Water, Salt, Citric Acid